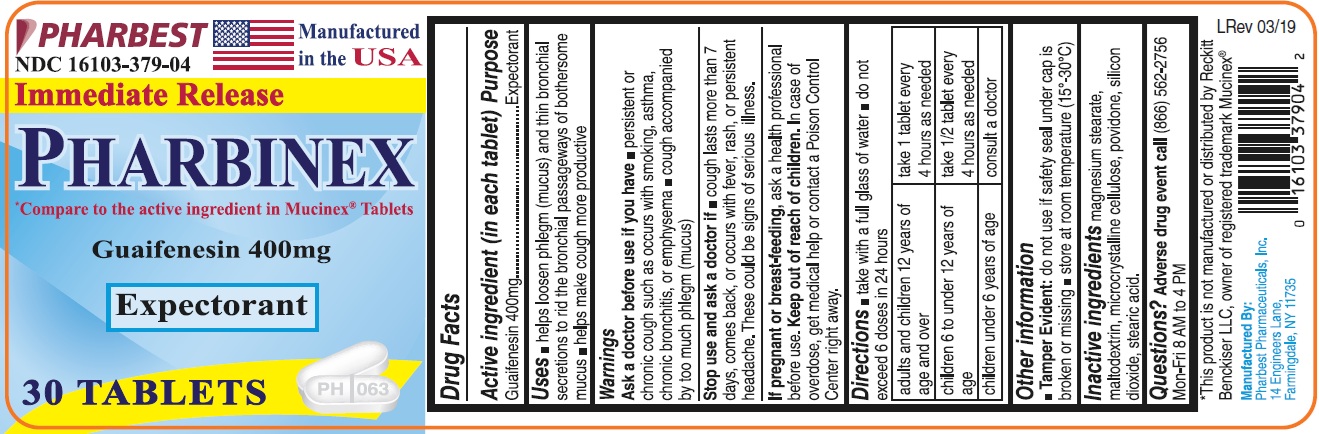 DRUG LABEL: GUAIFENESIN
NDC: 16103-379 | Form: TABLET
Manufacturer: Pharbest Pharmaceuticals, Inc.
Category: otc | Type: HUMAN OTC DRUG LABEL
Date: 20251224

ACTIVE INGREDIENTS: GUAIFENESIN 400 mg/1 1
INACTIVE INGREDIENTS: MAGNESIUM STEARATE; MALTODEXTRIN; CELLULOSE, MICROCRYSTALLINE; POVIDONE, UNSPECIFIED; SILICON DIOXIDE; STEARIC ACID

Drug Facts

Active Ingredient (in each tablet)

Guaifenesin 400mg

Purpose

Expectorant

Uses

- helps loosen phlegm (mucus) and thin bronchial secretions to rid the bronchial passageways of bothersome mucus
- helps make cough more productive

Warnings

Ask doctor before use if you have

- persistent or chronic cough such as occurs with smoking, asthma, chronic bronchitis, or emphysema
- cough accompanied by too much phlegm (mucus)

Stop use and ask a doctor if

- cough lasts more than 7 days, comes back, or occurs with fever, rash, or persistent headache.

These could be signs of serious illness.

If pregnant or breast-feeding,

ask a health professional before use.

Keep out of reach of children.

In case of overdose, get medical help or contact a Poison Control Center right away.

Directions

- take with a full glass of water
- do not exceed 6 doses in 24 hours

adults and children 12 years of age and over | take 1 tablet every 4 hours as needed
children 6 to under 12 years of age | take ½ tablet every 4 hours as needed
children under 6 years of age | consult a doctor

Other information

- store at room temperature (15°-30°C)
- Tamper Evident: do not use if safety seal under cap is broken or missing

Inactive ingredients

magnesium stearate, maltodextrin, microcrystalline cellulose, povidone, silicon dioxide, stearic acid.

Questions?

Adverse drug event call (866) 562-2756 Mon-Fri 8 AM to 4 PM

PACKAGE LABEL

PHARBEST

NDC 16103-379-04

Manufactured in the USA

Immediate Release

PHARBINEX

*COMPARE TO the active ingredient in MUCINEX® Tablets

Guaifenesin 400mg

Expectorant

30 TABLETS